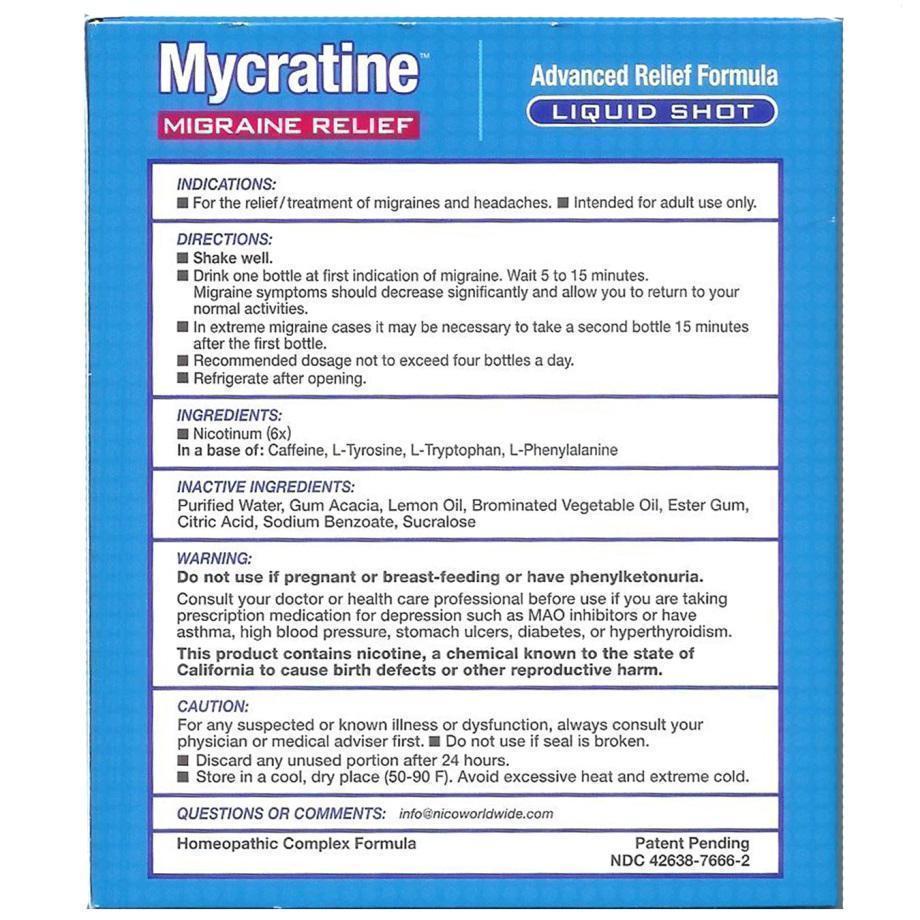 DRUG LABEL: Mycratine
NDC: 42638-7666 | Form: LIQUID
Manufacturer: Nico Worldwide, Inc.
Category: homeopathic | Type: HUMAN OTC DRUG LABEL
Date: 20131218

ACTIVE INGREDIENTS: NICOTINE 6 [hp_X]/60 mL; TYROSINE 30 mg/60 mL; PHENYLALANINE 20 mg/60 mL; TRYPTOPHAN 40 mg/60 mL; CAFFEINE 85 mg/60 mL
INACTIVE INGREDIENTS: WATER 59150 mg/60 mL; SUCRALOSE 10 mg/60 mL; SODIUM CITRATE 45 mg/60 mL; SODIUM BENZOATE 10 mg/60 mL

Mycratine Label Description

ACTIVE INGREDIENT

Ingredients

- Nicotinum (6x)

In a base of: Caffeine, L-Tyrosine, L-Tryptophan, L-Phenylalanine

PURPOSE

Mycratine Migraine Relief

Advanced Relief Formula

Liquid Shot

Keep out of reach of children.

Indications:

For the relief/treatment of migraines and headaches

Intended for adult use only

Warning:

Do not use if pregnant or breast-feeding or have pheylketonuria.

Consult your doctor or health care professional before use if you are taking prescription medication for depression such as MAO inhibitors or have asthma, high blood pressure, stomach ulcers, diabetes, or hyperthyroidism.

This product contains nicotine, a chemical known to the state of California to cause birth defects or other reproductive harm.

Caution:

- For any suspected or known illness or dysfunction, always consult your physician or medical adviser first.
- Do not use if seal is broken.
- Discard any unused portion after 24 hours.
- Store in a cool, dry place (50-90 F). Avoid excessive heat and extreme cold.

Directions:

- Shake well.
- Drink one bottle at first indication of migraine. Wait 5 to 15 minutes. Migraine symptoms should decrease significantly and allow you to return to your normal activities.
- In extreme migraine cases it may be necessary to take a second bottle 15 minutes after the first bottle.
- Recommended dosage not to exceed four bottles a day.
- Refrigerate after opening.

Inactive Ingredients:

purified water, gum acacia, lemon oil, brominated vegetable oil, ester gum, citric acid, sodium benzoate, sucralose.

Questions or comments: info@nicoworldwide.com

Homeopathic Complex Formula

Patent Pending

NDC 42638-7666-2